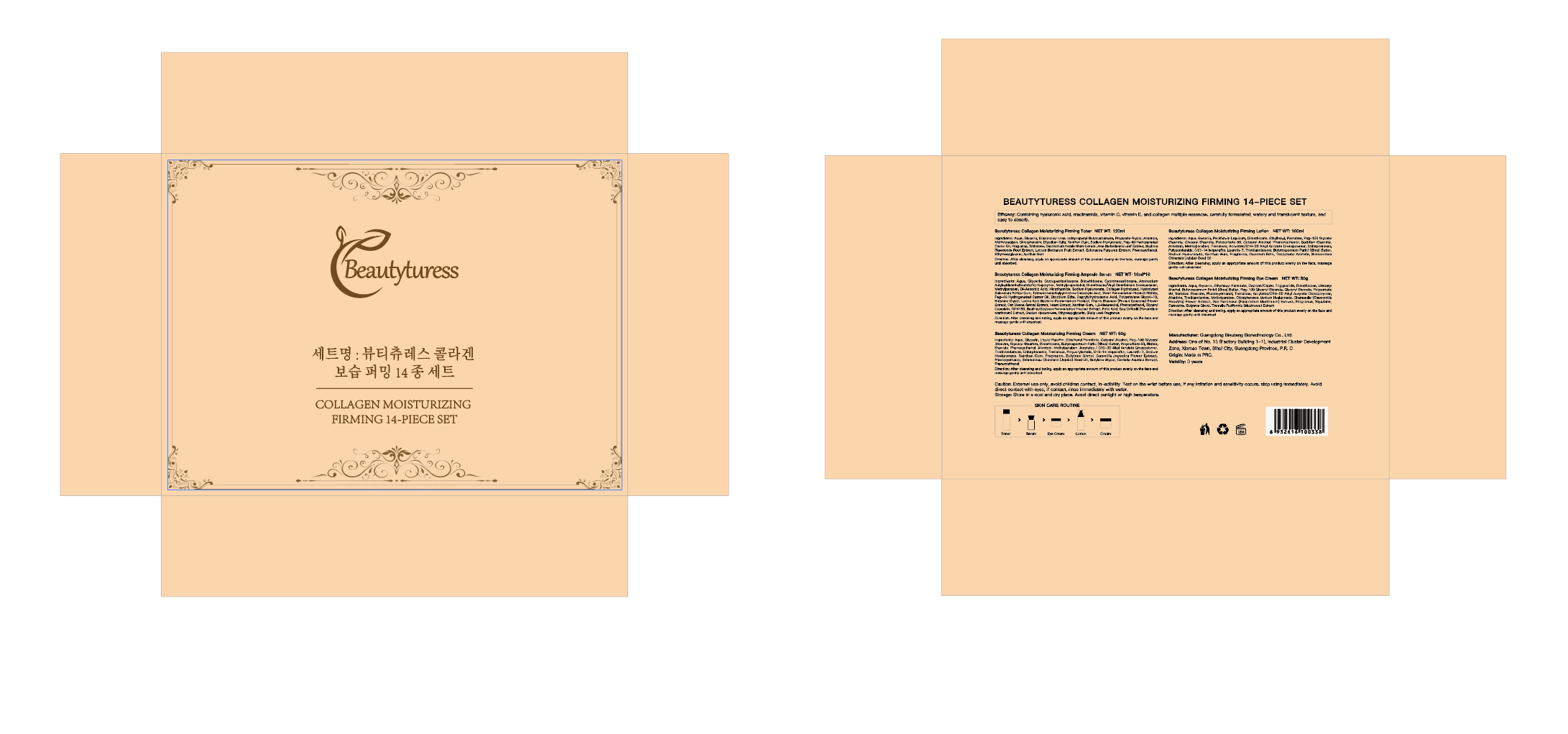 DRUG LABEL: Beautyturess Collagen Moisturizing Firming 14-Piece Set
NDC: 84753-033 | Form: LIQUID
Manufacturer: Guangdong Bisutang Biotechnology Co., Ltd.
Category: otc | Type: HUMAN OTC DRUG LABEL
Date: 20250115

ACTIVE INGREDIENTS: GLYCERIN 3 g/120 mL
INACTIVE INGREDIENTS: GLYCYRRHIZA URALENSIS; CARBOMER; XANTHAN GUM; MINERAL OIL; MANNITOL; ADIPIC ACID; DIPROPYLENE GLYCOL; WATER; 1,2-BUTANEDIOL

ACTIVE INGREDIENT

GLYCERIN

PURPOSE

After cleansing andtoning, take an appropriate amount ofthis product and apply it evenly on theface, massage until absorbed

Ask Doctor

If you have a history of skin allergies or have sensitive skin, it is advisable to consult a doctor before using this product.

DOSAGE AND ADMINISTRATION

Apply once daily to clean face and neck, avoiding the eye area

WHEN USING

Avoid contact with eyes and broken skin. If redness, swelling, or irritation occurs, discontinue use immediately and seek medical advice.

WARNINGS

Risk InformationFor external use only
Mention de risquesPour usage externe seulement
Do not use on damaged or broken skin.
Ne pas utiliser sur la peau endommagée ou avec des lésions
If rash occurs, discontinue use and consult a health care practitioner.
En présence d'une éruption cutanée, cesser l'utilisation et consulter un praticien de soins de santé
When using this product keep out of eyes. Rinse with water to remove.
Eviter tout contact avec les yeux. Rincer a l'eau le cas échéant
Keep out of reach of children. If swallowed, get medical help or contact a Poison Control Center right away.
Tenir hors de portée des enfants
En cas d'ingestion, consulter un médecin ou appeler un centre antipoison immédiatement.

INDICATIONS AND USAGE

Temporarily protects and helps relieve dry or cracked skin
Beneficlal for face, hands, body, and legs

Keep out of reach of children. If swallowed, get medical help or contact a Poison Control Center right away.
Tenir hors de portée des enfants
En cas d'ingestion, consulter un médecin ou appeler un centre antipoison immédiatement.

INACTIVE INGREDIENT

.Water · Butylglycerin ·Glycyrrhiza Uralensis (Licorice) Sprout ExtractRosa Damascena Flower-Lactobacillus/Tremella Fuciformis Extract FermentFiltrate, Carbomer·Xanthan Gum·Mineral Oil · Mannitol· Butanediol/AdipicAcid Copolymer·And Other ingredients